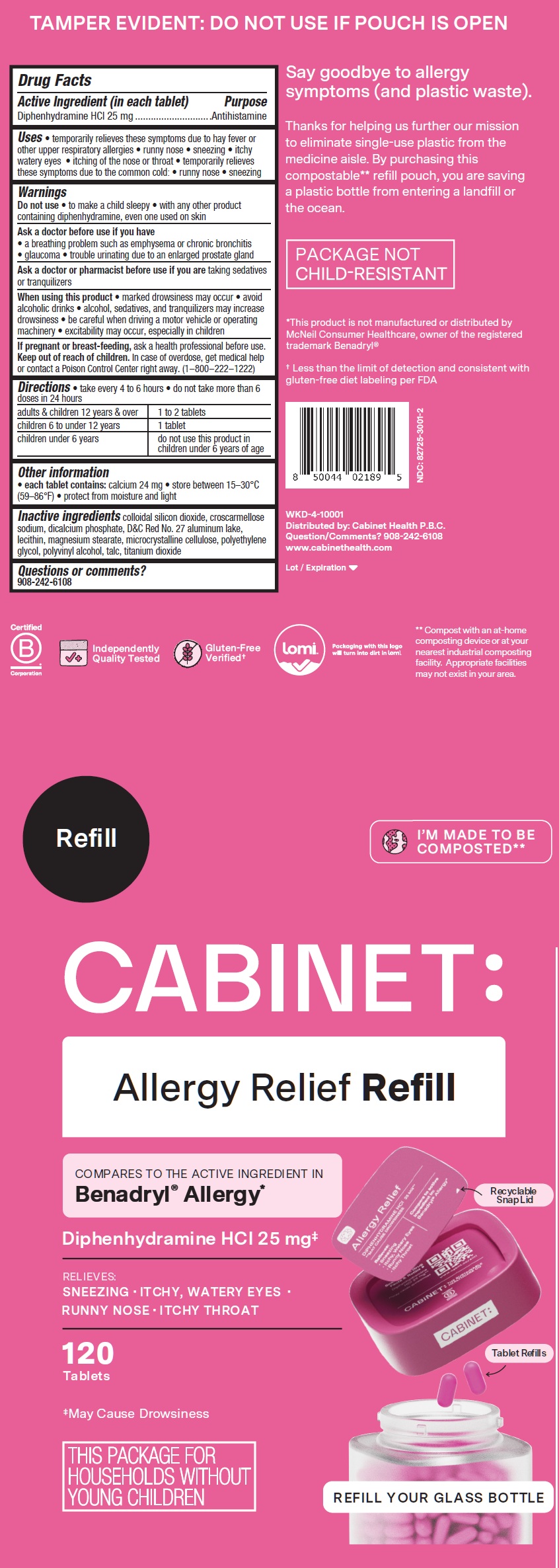 DRUG LABEL: Cabinet Allergy Relief Refill Diphenhydramine HCI
NDC: 82725-3001 | Form: TABLET
Manufacturer: Cabinet Health P.B.C.
Category: otc | Type: HUMAN OTC DRUG LABEL
Date: 20250703

ACTIVE INGREDIENTS: DIPHENHYDRAMINE HYDROCHLORIDE 25 mg/1 1
INACTIVE INGREDIENTS: SILICON DIOXIDE; CROSCARMELLOSE SODIUM; DICALCIUM PHOSPHATE; D&C RED NO. 27 ALUMINUM LAKE; MAGNESIUM STEARATE; MICROCRYSTALLINE CELLULOSE; POLYETHYLENE GLYCOL, UNSPECIFIED; POLYVINYL ALCOHOL, UNSPECIFIED; TALC; TITANIUM DIOXIDE

Cabinet Allergy Relief Refill, Diphenhydramine HCI

Active Ingredient (in each tablet)

Diphenhydramine HCl 25 mg

Purpose

Antihistamine

Uses

• temporarily relieves these symptoms due to hay fever or other upper respiratory allergies • runny nose • sneezing • itchy watery eyes • itching of the nose or throat • temporarily relieves these symptoms due to the common cold: • runny nose • sneezing

Warnings

Do not use

• to make a child sleepy • with any other product containing diphenhydramine, even one used on skin

Ask a doctor before use if you have

• a breathing problem such as emphysema or chronic bronchitis • glaucoma • trouble urinating due to an enlarged prostate gland

Ask a doctor or pharmacist before use if you are

taking sedatives or tranquilizers

When using this product

• marked drowsiness may occur • avoid alcoholic drinks • alcohol, sedatives, and tranquilizers may increase drowsiness • be careful when driving a motor vehicle or operating machinery • excitability may occur, especially in children

If pregnant or breast-feeding,

ask a health professional before use.

Keep out of reach of children.

In case of overdose, get medical help or contact a Poison Control Center right away. (1-800-222-1222)

Directions

- take every 4 to 6 hours • do not take more than 6 doses in 24 hours

adults & children 12 years & over | 1 to 2 tablets
children 6 to under 12 years | 1 tablet
children under 6 years | do not use this product in children under 6 years of age

Other information

• each tablet contains:calcium 24 mg • store between 15–30°C (59–86°F) • protect from moisture and light

Inactive ingredients

colloidal silicon dioxide, croscarmellose sodium, dicalcium phosphate, D&C Red No. 27 aluminum lake, lecithin, magnesium stearate, microcrystalline cellulose, polyethylene glycol, polyvinyl alcohol, talc, titanium dioxide

Questions or comments?

908-242-6108